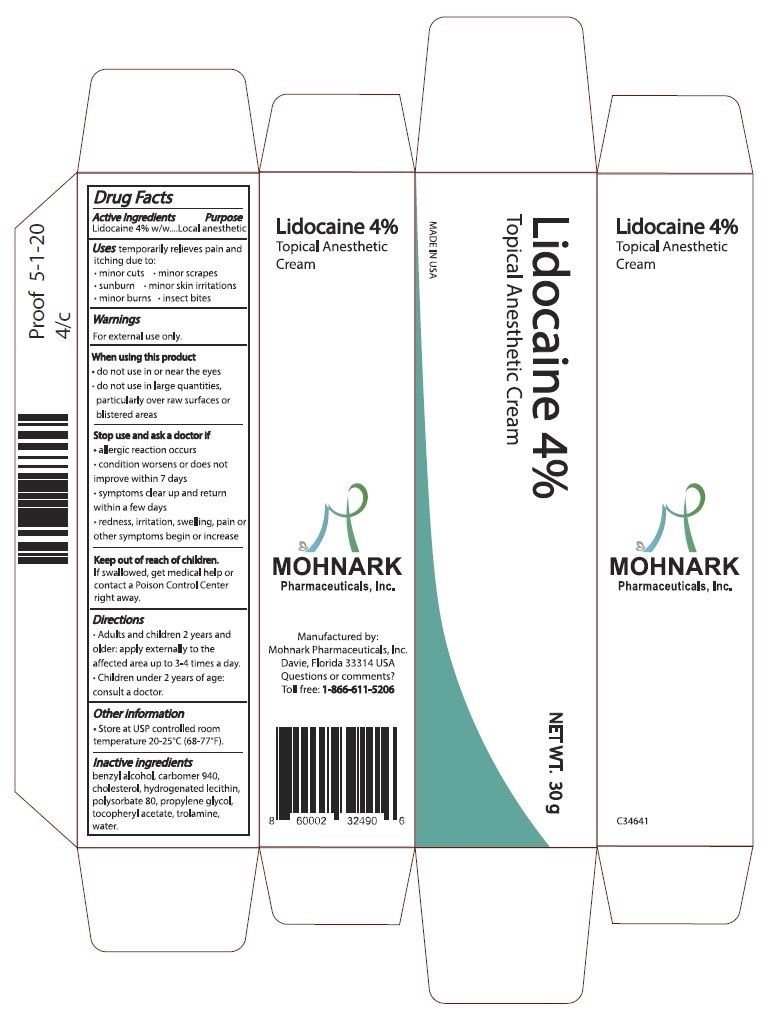 DRUG LABEL: Lidocaine 4% Topical Anesthetic Cream
NDC: 73715-001 | Form: CREAM
Manufacturer: Mohnark Pharmaceuticals Inc.
Category: otc | Type: HUMAN OTC DRUG LABEL
Date: 20250720

ACTIVE INGREDIENTS: LIDOCAINE 4.27 g/100 g
INACTIVE INGREDIENTS: POLYSORBATE 80 2 g/100 g; WATER 80.48 g/100 g

Lidocaine 4% Topical Anesthetic Cream with Vit E

Active Ingredients

Lidocaine 4% w/w

Purpose

Topical Anesthetic

Uses temporarily relieves pain and itching due to:

- minor cuts
- minor scrapes
  - sunburn
  - minor skin irritations
  - minor burns
  - insect bites

Warnings

For external use only

When using this product

- do not use in or near the eyes
- do not use in large quantities, particularly over raw surfaces or blistered areas

Stop use and ask a doctor if

- allergic reaction occurs
- condition worsens or does not improve within 7 days
- symptoms clear up and return within a few days
- redness, irritation, swelling, pain or other symptoms begin or increase

Keep out of reach of children

if swallowed, get medical help or contact a Poison Control Center right away

Directions

- Adults and children 2 years and older: apply externally to the affected area up to 3-4 times a day.
- Children under 2 years of age: consult a doctor

Other information

- Store at USP controlled room temperature 20-25oC (68-77oF).

Inactive ingredients

benzyl alcohol, cabomer 940, cholesterol, hydrogenated lecithin, polysorbate 80, propylene glycol, tocopheryl acetate, trolamine, water

Dosage

40 milligrams/gram per application

Usage

- Adults and children 2 years and older: apply externally to the affected area up to 3-4 times a day.
- Children under 2 years of age: consult a doctor